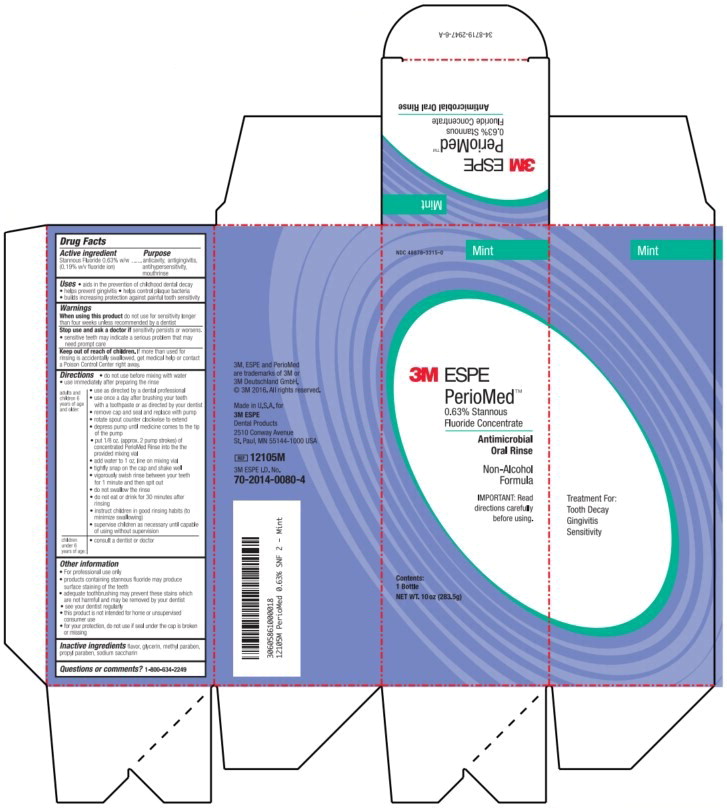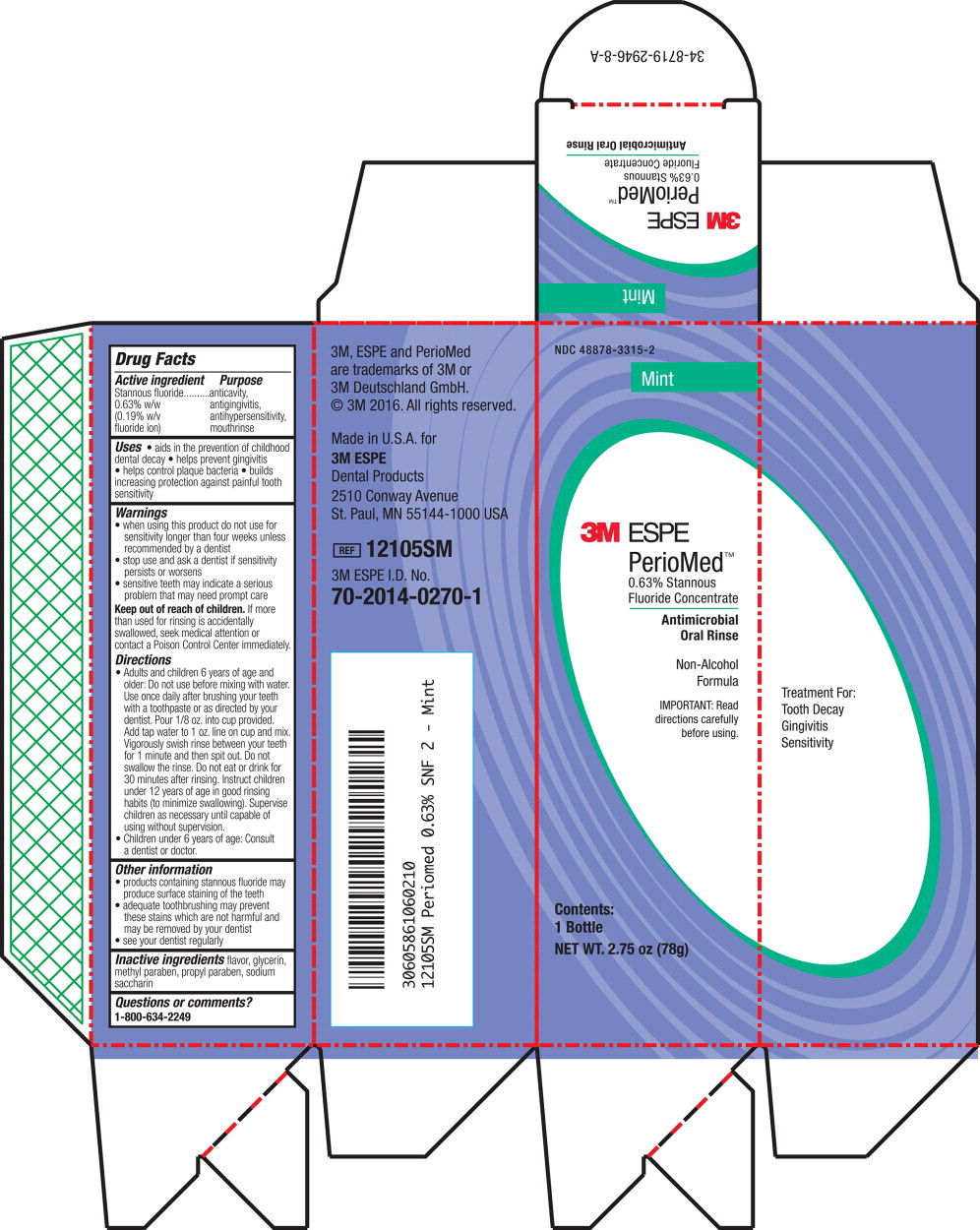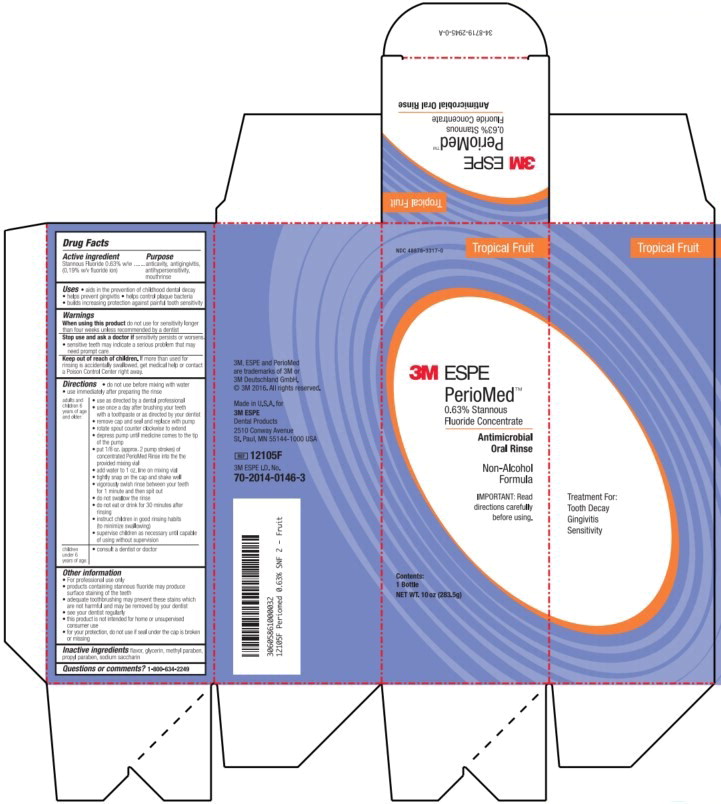 DRUG LABEL: PerioMed
NDC: 48878-3315 | Form: RINSE
Manufacturer: Solventum US LLC
Category: otc | Type: HUMAN OTC DRUG LABEL
Date: 20240801

ACTIVE INGREDIENTS: Stannous Fluoride 1.53 mg/1 g
INACTIVE INGREDIENTS: Glycerin; Methylparaben; Propylparaben; Saccharin

Drug Facts

Active ingredient

Stannous fluoride 0.63% w/w (0.19% w/v flouride ion)

Purpose

anticavity, antigingivitis, antihypersensitivity, mouthrinse

Uses

- aids in the prevention of childhood dental decay
- helps prevent gingivitis
- helps control plaque bacteria
- builds increasing protection against painful tooth sensitivity

Warnings

- When using this product do not use for sensitivity longer than four weeks unless recommended by a dentist.

- Stop use and ask a doctor if sensitivity persists or worsens.
- Sensitive teeth may indicate a serious problem that may need prompt care.

- Keep out of reach of children. If more than used for rinsing is accidentally swallowed, get medical help or contact a Poison Control Center right away.

Directions

adults and children 6 years of age and older:

- do not use before mixing with water
- use immediately after preparing the rinse
- use as directed by a dental professional
- use once a day after brushing your teeth with a toothpaste or as directed by your dentist
- remove cap and seal and replace with pump
- rotate spout counter clockwise to extend
- depress pump until medicine comes to the tip of the pump
- put 1/8 oz. (approx. 2 pump strokes) of concentrated PerioMed Rinse into the provided mixing vial
- add water to 1 oz. line on mixing vial
- tightly snap on the cap and shake well
- vigorously swish rinse between your teeth for 1 minute and then spit out
- do not swallow the rinse
- do not eat or drink for 30 minutes after rinsing
- instruct children in good rinsing habits (to minimize swallowing)
- supervise children as necessary until capable of using without supervision

children under 6 years of age:

- consult a dentist or doctor

Other information

- For professional use only
- products containing stannous fluoride may produce surface staining of the teeth
- adequate toothbrushing may prevent these stains which are not harmful and may be removed by your dentist
- see your dentist regularly
- this product is not intended for home or unsupervised consumer use
- for your protection, do not use if seal under the cap is broken or missing

Inactive ingredients

flavor, glycerin, methyl paraben, propyl paraben, sodium saccharin

Questions or comments?

1-800-634-2249

Principal Display Panel – Box Label (Mint – 283.5 g)

NDC 48878-3315-0

Mint

3M ESPE

PerioMed™

0.63% Stannous

Fluoride Concentrate

Antimicrobial

Oral Rinse

Non-Alcohol

Formula

IMPORTANT: Read

directions carefully

before using.

Contents:

1 Bottle

NET WT. 10 oz (283.5g)

Principal Display Panel – Box Label (Mint – 78 g)

NDC 48878-3315-2

Mint

3M ESPE

PerioMed™

0.63% Stannous

Fluoride Concentrate

Antimicrobial

Oral Rinse

Non-Alcohol

Formula

IMPORTANT: Read

directions carefully

before using.

Contents:

1 Bottle

NET WT. 2.75 oz (78g)

Principal Display Panel – Box Label (Tropical Fruit – 283.5 g)

NDC 48878-3317-0

Tropical Fruit

3M ESPE

PerioMed™

0.63% Stannous

Fluoride Concentrate

Antimicrobial

Oral Rinse

Non-Alcohol

Formula

IMPORTANT: Read

directions carefully

before using.

Contents:

1 Bottle

NET WT. 10 oz (283.5g)